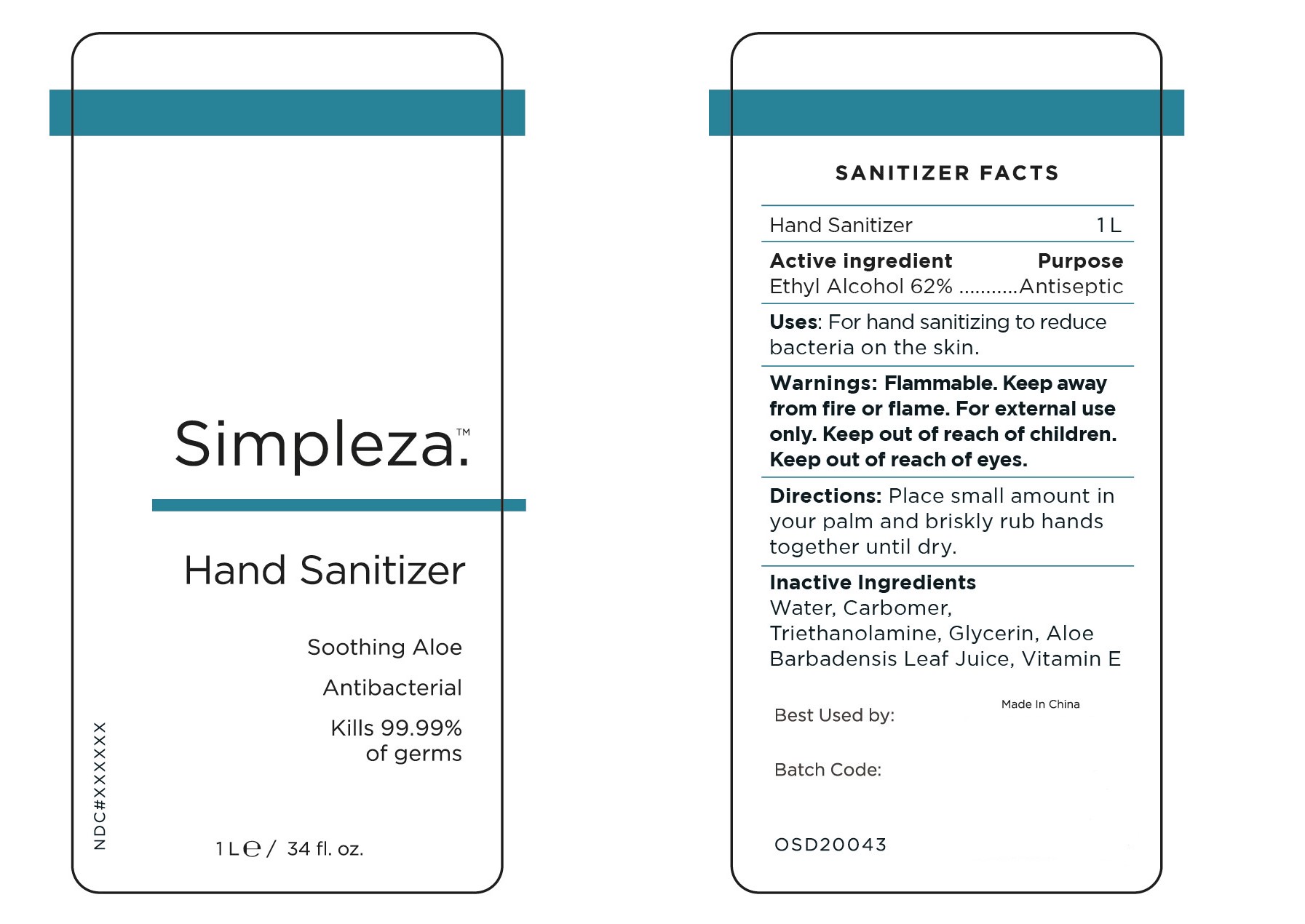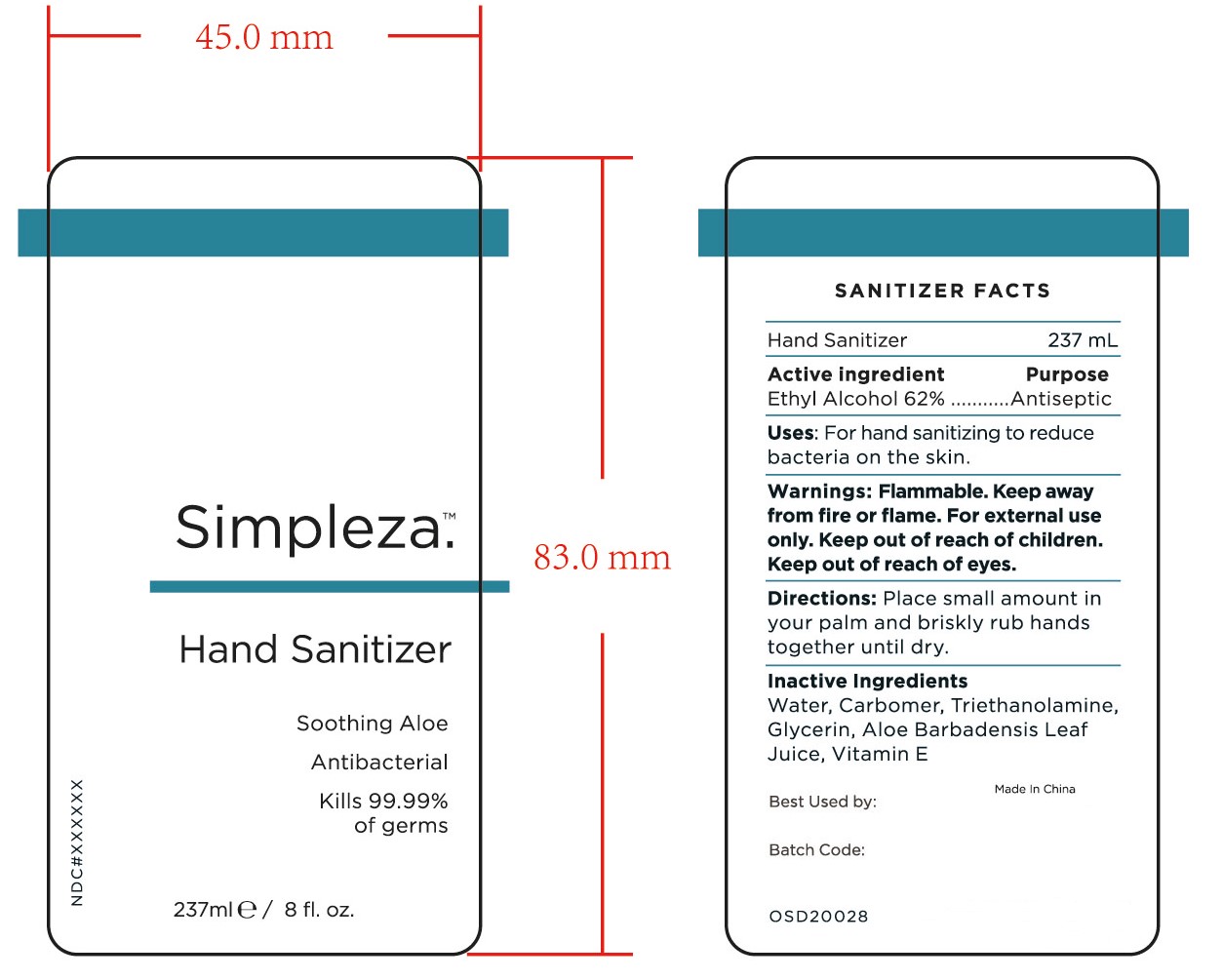 DRUG LABEL: HAND SANITIZER
NDC: 47993-239 | Form: GEL
Manufacturer: NINGBO JIANGBEI OCEAN STAR TRADING CO.,LTD
Category: otc | Type: HUMAN OTC DRUG LABEL
Date: 20201104

ACTIVE INGREDIENTS: ALCOHOL 62 g/112 mL
INACTIVE INGREDIENTS: CARBOMER 940 12 g/112 mL; TRIETHANOLAMINE BENZOATE; GLYCERIN 2 g/112 mL; TOCOPHEROL; WATER; ALOE VERA LEAF

47993-239

Active ingredients

Ethyl Alcohol 62%

PURPOSE

Antiseptic

Uses：

For hand sanitizing to readuce bacteria on the skin.

Warnings:

Flammable. Keep away from fire or flame. For external use only. Keep out of reach of children. Keep out of reach of eyes.

Keep out of reach of children.

Directions:

Place small amount in your palm and briskly rub hands together until dry.

Inactive Ingredients:

Water,Carbomer,Triethanolamine,Glycerin,Aloe Barbadensis Leaf Juice,Vitamin E